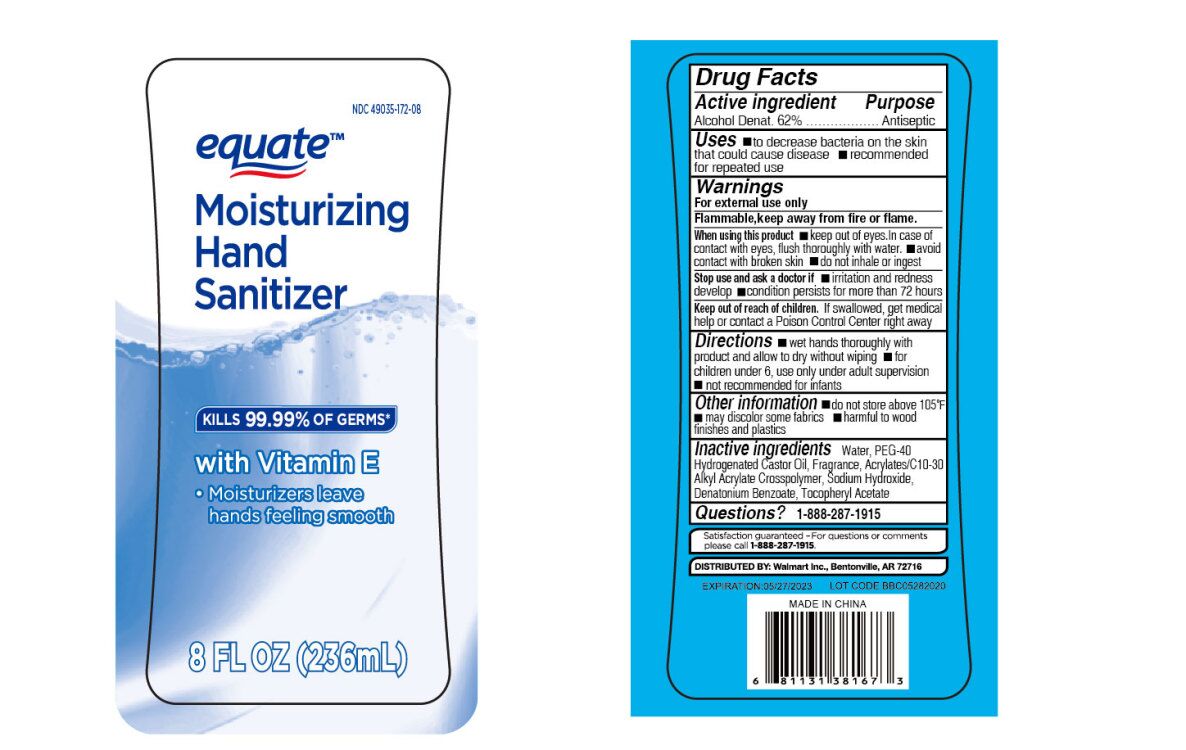 DRUG LABEL: Hand Sanitizer
NDC: 76383-014 | Form: LIQUID
Manufacturer: BBC GROUP LIMITED
Category: otc | Type: HUMAN OTC DRUG LABEL
Date: 20200911

ACTIVE INGREDIENTS: ALCOHOL 62 mL/100 mL
INACTIVE INGREDIENTS: .ALPHA.-TOCOPHEROL ACETATE; DENATONIUM BENZOATE; WATER; CARBOMER INTERPOLYMER TYPE A (55000 CPS); POLYOXYL 40 HYDROGENATED CASTOR OIL; SODIUM HYDROXIDE

Hand Sanitizer with VitE

Active ingredient

Alcohol Denat. 62%

Purpose

Antiseptic

Uses

■ to decrease bacteria on the skin that could cause disease ■ recommended for repeated use

Warnings

For external use only. Flammable, keep away from fire or flame

When using this product

■ keep out of eyes. In case of contact with eyes, flush thoroughly with water. ■ avoid contact with broken skin ■ do not inhale or ingest

Stop use and ask a doctor if

■ irritation and redness develop ■ condition persists for more than 72 hours

Keep out of reach of children

If swallowed, get medical help or contact a Poison Control Center right away.

Directions

■ wet hands thoroughly with product and allow to dry without wiping ■ for children under 6, use only under adult supervision ■ not recommended for infants

Other information

■ do not store above 105ºF ■ may discolor some fabrics ■ harmful to wood finishes and plastics

Inactive ingredients

Water, PEG-40 Hydrogenated Castor Oil, Fragrance, Acrylates/C10-30 Alkyl Acrylate Crosspolymer, Sodium Hydroxide, Denatonium Benzoate, Tocopheryl Acetate

Questions?

1-888-287-1915